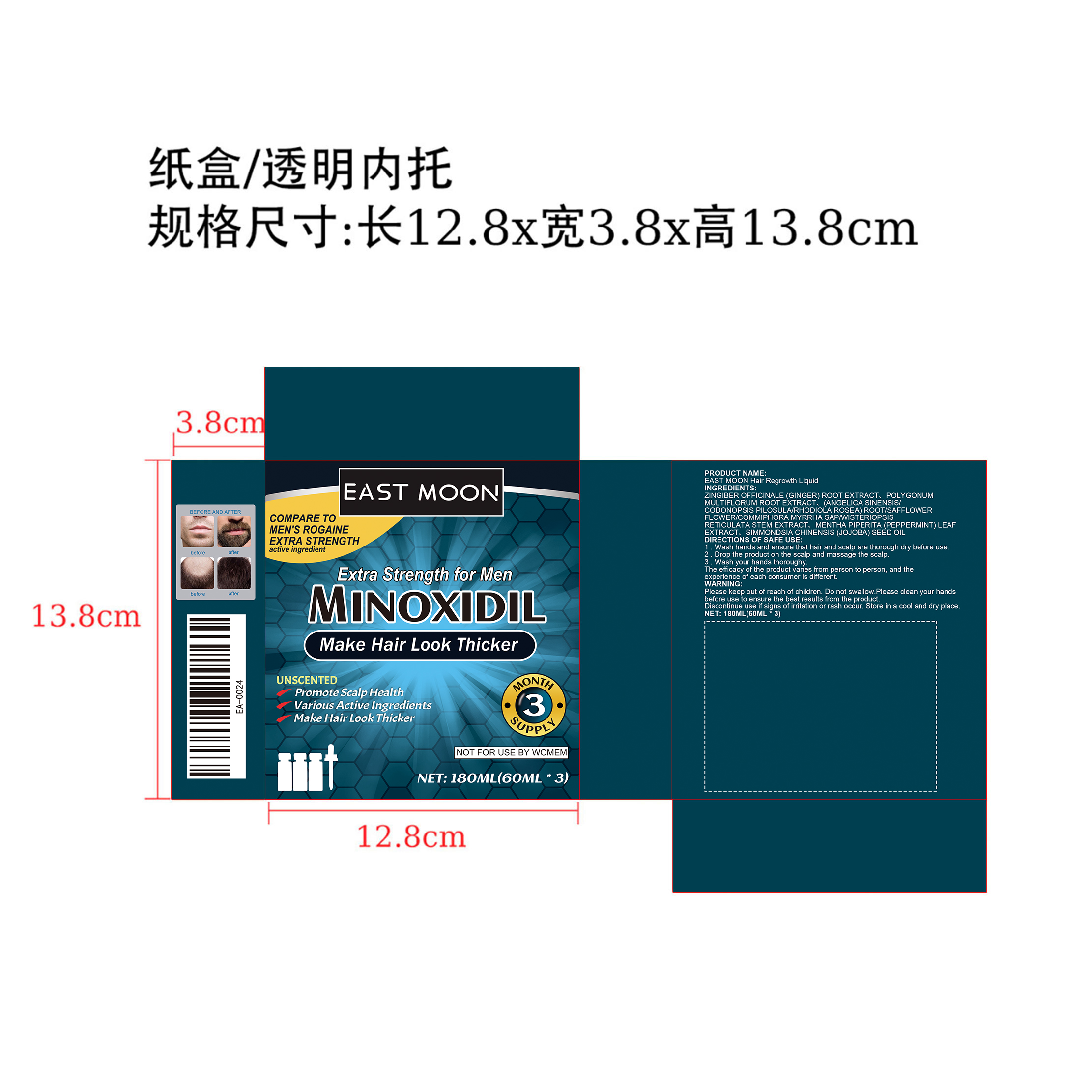 DRUG LABEL: hair growth solution
NDC: 84778-017 | Form: LIQUID
Manufacturer: Guangzhou Yixin Cross-border E-commerce Co., Ltd.
Category: otc | Type: HUMAN OTC DRUG LABEL
Date: 20241028

ACTIVE INGREDIENTS: ZINGIBER OFFICINALE (GINGER) ROOT EXTRACT 20 g/20 mL
INACTIVE INGREDIENTS: MENTHA PIPERITA (PEPPERMINT) LEAF EXTRACT; POLYGONUM MULTIFLORUM ROOT EXTRACT; SIMMONDSIA CHINENSIS (JOJOBA) SEED OIL

COMPONENTS

Zingiber Officinale (Ginger) Root Extract 20g

PURPOSE

to regrow hair on the top of the scalp

INDICATIONS AND USAGE

apply one mL with dropper 2 times a day directly onto the scalp in the hair loss area

using more or more often will notimprove results

continued use is necessary to increase and keep your hair regrowth, or hair loss willbegin again

WARNINGS

For external use only.

Flammable: Keep away from fire or flame

DOSAGE AND ADMINISTRATION

For external use only

DO NOT USE

you have no family history of hair loss

your hairloss is sudden and/or patchy

you do not know the reason for your hair loss

you are under 18 years of age.

Do not use on babies and children.

your scalp is red, inflamed,infected, irritated, or painfulyou use other medicines on the scalp

WHEN USING

do not apply on other parts of the body

avoid contact with the eyes. in case of accidental contact, rinse eyes with large amountsof cool tap water.

some people have experienced changes in hair color and/or texture

it takes time to regrow hair. Results may occur at 2 months with twice a day usage. For somemen, you mav need to use this product for at least 4 months before vou see results.

the amount of hair regrowth is diferent for each person. This product will not work for all men.

STOP USE

chest pain, rapid heartbeat, faintness, or dizziness occurs

sudden.unexplained weight gain occurs

your hands or feet swell

scalo irritation or redness occurs

unwanted facial hair growth occurs

you do not see hair regrowth in 4 months

Keep out of reach of children.lf swallowed, get medical help or contacta Poison Control Center right away

INACTIVE INGREDIENT

Polygonum Multiflorum Root

Mentha Piperita (Peppermint) Leaf Extract

Simmondsia Chinensis (Jojoba) Seed Oil

Angelica Sinensis/CodonopsisPilosula/Rodola Rosea Root Extract